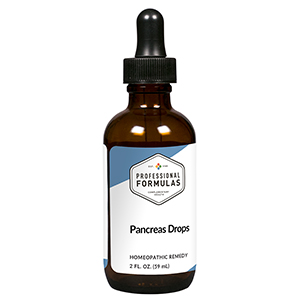 DRUG LABEL: Pancreas Drops
NDC: 63083-5020 | Form: LIQUID
Manufacturer: Professional Complementary Health Formulas
Category: homeopathic | Type: HUMAN OTC DRUG LABEL
Date: 20190815

ACTIVE INGREDIENTS: ARTEMISIA ANNUA FLOWERING TOP 3 [hp_X]/59 mL; FOENICULUM VULGARE FRUIT 3 [hp_X]/59 mL; GLYCYRRHIZA GLABRA 3 [hp_X]/59 mL; ACHILLEA MILLEFOLIUM WHOLE 3 [hp_X]/59 mL; SYZYGIUM CUMINI SEED 3 [hp_X]/59 mL; BILBERRY 3 [hp_X]/59 mL; ACETIC ACID 4 [hp_X]/59 mL; MARSDENIA CUNDURANGO WHOLE 4 [hp_X]/59 mL; KIDNEY BEAN 4 [hp_X]/59 mL; SMILAX ORNATA ROOT 4 [hp_X]/59 mL; GENTIANA LUTEA ROOT 6 [hp_X]/59 mL; BOS TAURUS PANCREAS 6 [hp_X]/59 mL; PANCRELIPASE AMYLASE 6 [hp_X]/59 mL; UREA 7 [hp_X]/59 mL; URIC ACID 7 [hp_X]/59 mL
INACTIVE INGREDIENTS: ALCOHOL; WATER

HPND

ACTIVE INGREDIENTS

Chamomilla 3X
Foeniculum vulgare 3X
Glycyrrhiza glabra 3X
Millefolium 3X
Syzygium jambolanum 3X
Vaccinium myrtillus 3X
Aceticum acidum 4X
Condurango 4X
Phaseolus 4X
Sarsaparilla 4X
Gentiana lutea 6X
Pancreas 6X
Pancreatinum 6X
Urea 7X
Uricum acidum 7X

QUESTIONS

Professional Formulas

PO Box 2034 Lake Oswego, OR 97035

INDICATIONS

For the temporary relief of mild abdominal or back pain, bloating, nausea or vomiting, diarrhea, loss of appetite, or feelings of discomfort or uneasiness.*

PURPOSE

*Claims based on traditional homeopathic practice, not accepted medical evidence. Not FDA evaluated.

WARNINGS

Severe or persistent symptoms may be serious. Consult a doctor promptly. Keep out of the reach of children. In case of overdose, get medical help or contact a poison control center right away. If pregnant or breastfeeding, ask a healthcare professional before use.

Keep out of the reach of children.

PREGNANCY OR BREAST FEEDING

If pregnant or breastfeeding, ask a healthcare professional before use.

DIRECTIONS

Place drops under tongue 30 minutes before/after meals. Adults and children 12 years and over: Take 10 drops up to 3 times per day. Consult a physician for use in children under 12 years of age.

OTHER INFORMATION

Tamper resistant. If seal is broken, do not use. After opening, close container tightly and store at room temperature away from heat.

INACTIVE INGREDIENTS

20% ethanol, purified water.

LABEL

Est 1985

Professional Formulas

Complementary Health

Pancreas Drops

Homeopathic Remedy

2 FL. OZ. (59 mL)